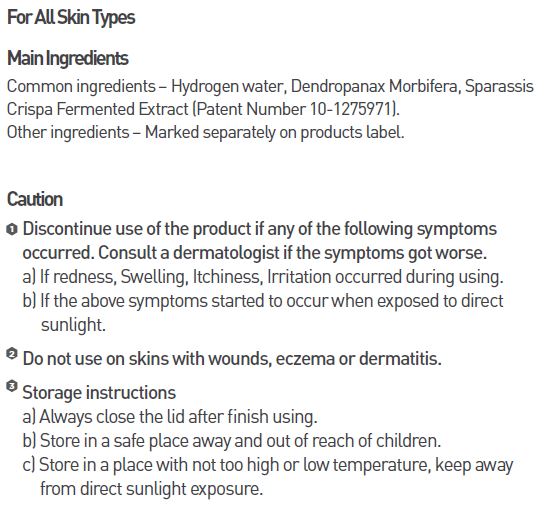 DRUG LABEL: MEDI HYDRO DP MIST
NDC: 70694-0005 | Form: LIQUID
Manufacturer: Inc MBG
Category: otc | Type: HUMAN OTC DRUG LABEL
Date: 20190124

ACTIVE INGREDIENTS: GLYCERIN 1 g/100 mL
INACTIVE INGREDIENTS: WATER; BUTYLENE GLYCOL

INDICATIONS AND USAGE

spray proper amount to the skin

Keep out of reach of children.

DOSAGE AND ADMINISTRATION

for external use only

WARNINGS

Discontinue use of the product if any of the following symptoms occurred. Consult a dermatologist if the symptoms got worse.
a) If redness, Swelling, Itchiness, Irritation occurred during using.
b) If the above symptoms started to occur when exposed to direct sunlight.
Do not use on skins with wounds, eczema or dermatitis.

Storage instructions
a) Always close the lid after finish using.
b) Store in a safe place away and out of reach of children.
c) Store in a place with not too high or low temperature, keep awayfrom direct sunlight exposure.

PURPOSE

for skin protectant

INACTIVE INGREDIENT

water, butylene glycol, xanthan gum, sodium carbomer, etc.

ACTIVE INGREDIENT

glycerin